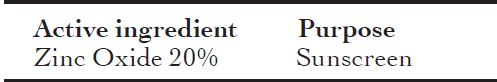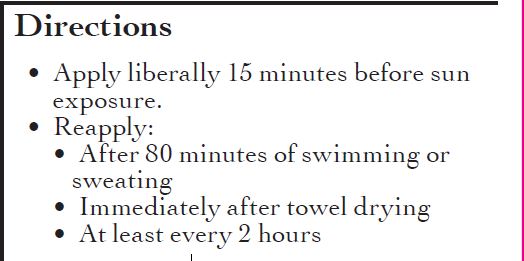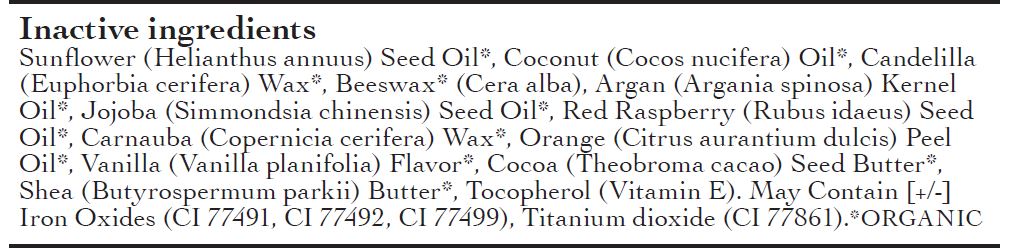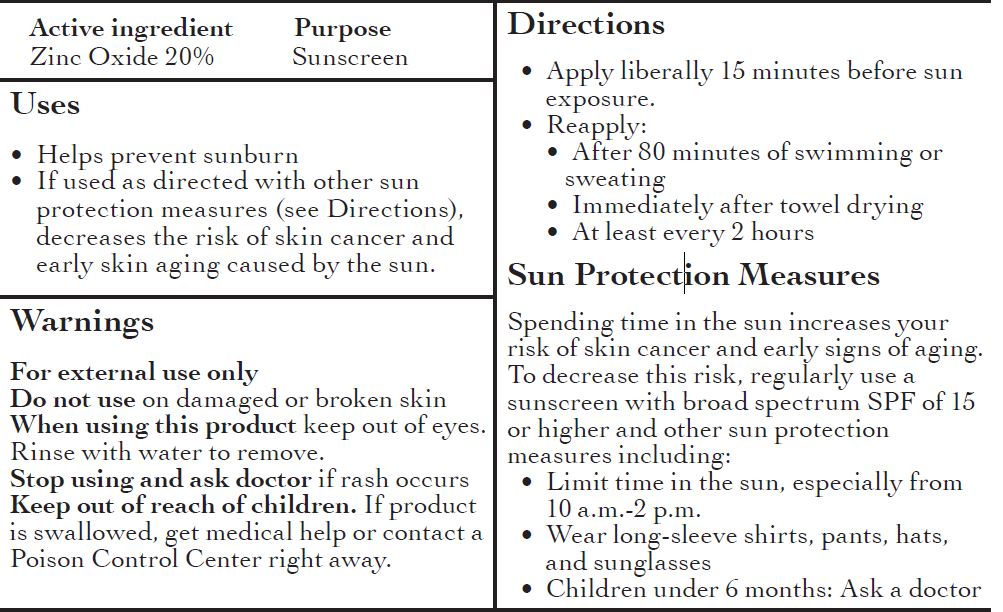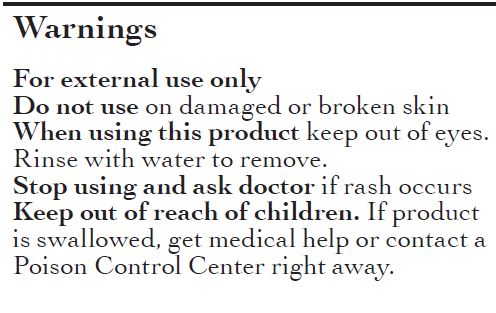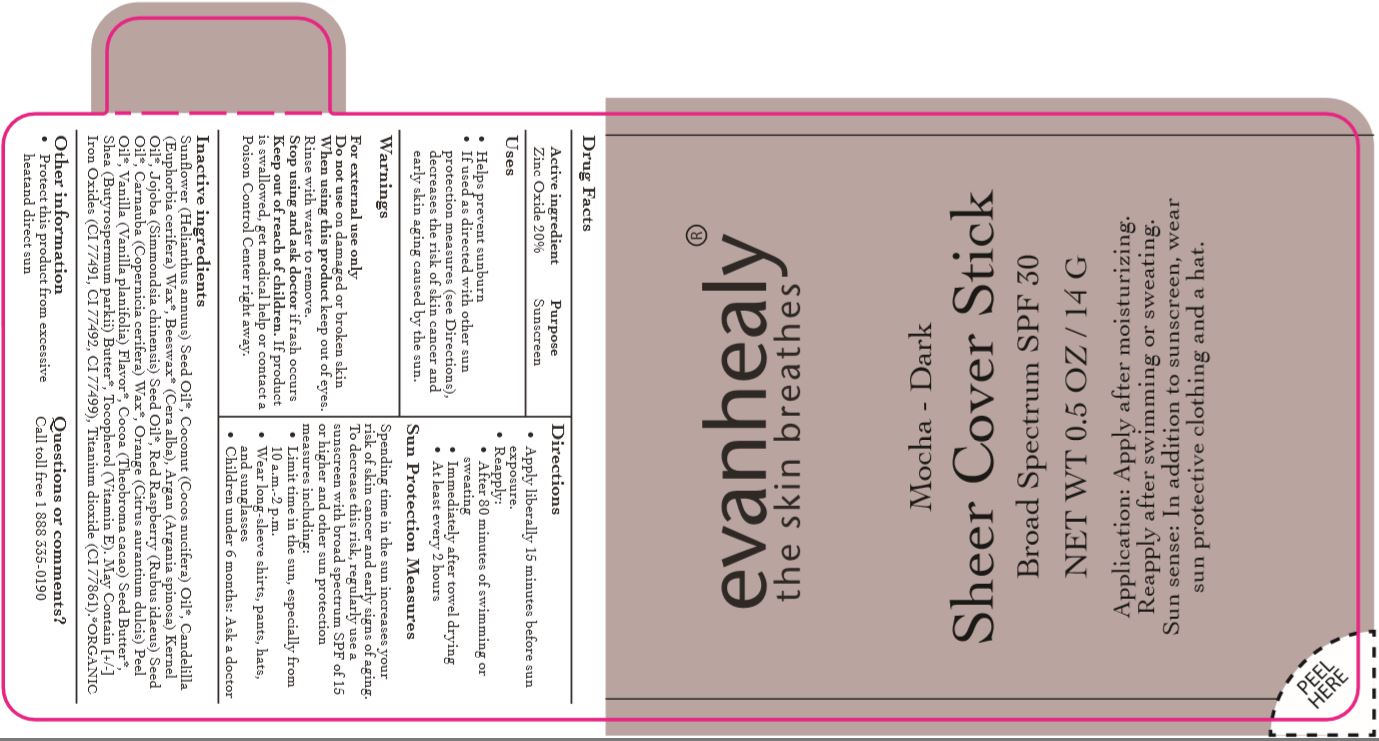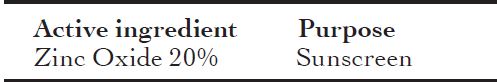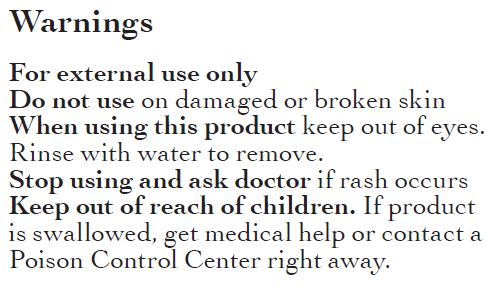 DRUG LABEL: SUNSCREEN
NDC: 62932-208 | Form: STICK
Manufacturer: Private Label Select Ltd CO
Category: otc | Type: HUMAN OTC DRUG LABEL
Date: 20191229

ACTIVE INGREDIENTS: ZINC OXIDE 20 g/100 g
INACTIVE INGREDIENTS: ORANGE OIL; JOJOBA OIL; COCONUT OIL; WHITE WAX; SUNFLOWER OIL; SHEA BUTTER; CANDELILLA WAX; CARNAUBA WAX; COCOA BUTTER; ARGAN OIL; .BETA.-TOCOPHEROL; RASPBERRY SEED OIL

Evanhealy Mocha - Dark Sheer Cover Stick SPF 30